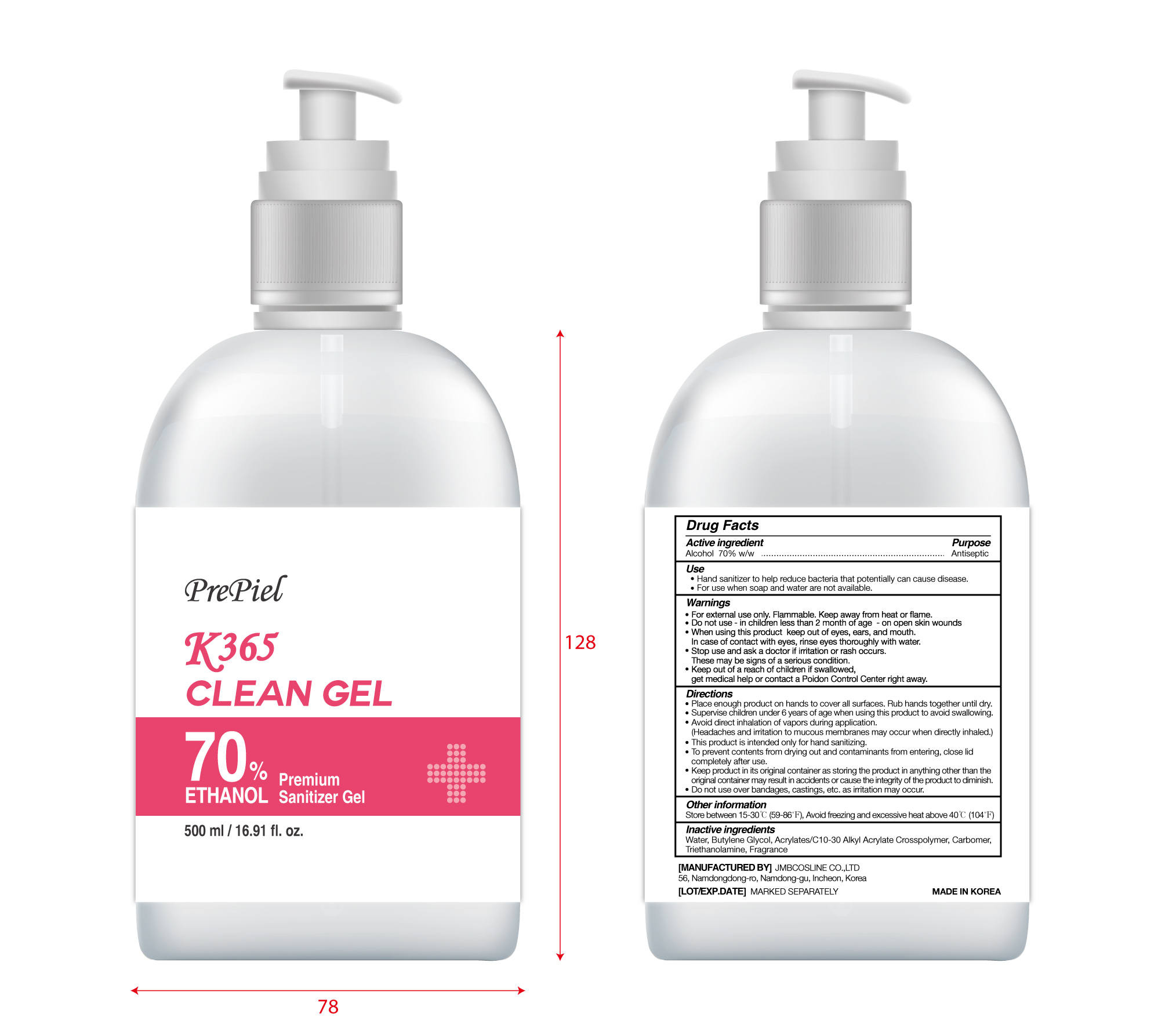 DRUG LABEL: Prepiel K365 CLEAN Gel
NDC: 90028-070 | Form: GEL
Manufacturer: JMB COSLINE CO.,LTD
Category: otc | Type: HUMAN OTC DRUG LABEL
Date: 20210209

ACTIVE INGREDIENTS: ALCOHOL 350 mL/500 mL
INACTIVE INGREDIENTS: WATER; CARBOMER HOMOPOLYMER, UNSPECIFIED TYPE; BUTYLENE GLYCOL; CARBOMER INTERPOLYMER TYPE A (55000 CPS); TROLAMINE

JMB COSLINE CO.,LTD - Prepiel K365 CLEAN GEL
90028-070-01
500 mL

Active ingredient

Alcohol 70% w/w .................................Antiseptic

Use

- Hand Sanitizer to help reduce bacteria that potentially can cause disease.
- For use when soap and water are not available.

Warnings

For external use only. Flammable. Keep away from heat or flame.

Do not use

■ in children less than 2 months of age ■ on open skin wounds

When using this product

keep out of eyes, ears, and mouth. In case of contact with eyes, rinse eyes thoroughly with water.

Stop use and ask a doctor

if irritation or rash occurs. These may be signs of a serious condition.

Keep out of reach of children

If swallowed, get medical help or contact a Poison Control Center right away.

Directions

■ Place enough product on hands to cover all surfaces. Rub hands together until dry.
■ Supervise children under 6 years of age when using this product to avoid swallowing.
■ Avoid direct inhalation of vapors during application.

(Headaches and irritation to mucous membranes may occur when directly inhaled.)
■ This product is intended only for hand sanitizing.
■ To prevent contents from drying out and contaminants from entering, close
lid completely after use.
■ Keep product in its original container as storing the product in anything other than

the original container may result in accidents or cause the integrity of the product to diminish.
■ Do not use over bandages, castings, etc. as irritation may occur.

Other information

■ Store between 15-30 °C (59-86 °F)
■ Avoid freezing and excessive heat above 40 °C (104 °F)

Inactive ingredients

Water, Butylene Glycol, Acrylates/C10-30 Alkyl Acrylate Crosspolymer, Carbomer,
Triethanolamine, Fragrance